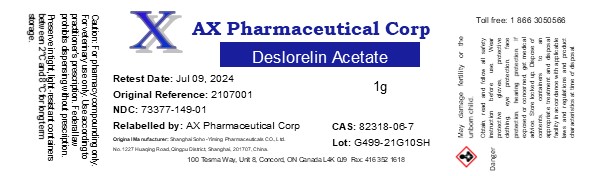 DRUG LABEL: Deslorelin Acetate
NDC: 73377-149 | Form: POWDER
Manufacturer: AX Pharmaceutical Corp
Category: other | Type: BULK INGREDIENT - ANIMAL DRUG
Date: 20260119

ACTIVE INGREDIENTS: DESLORELIN ACETATE 1 g/1 g

Deslorelin Acetate